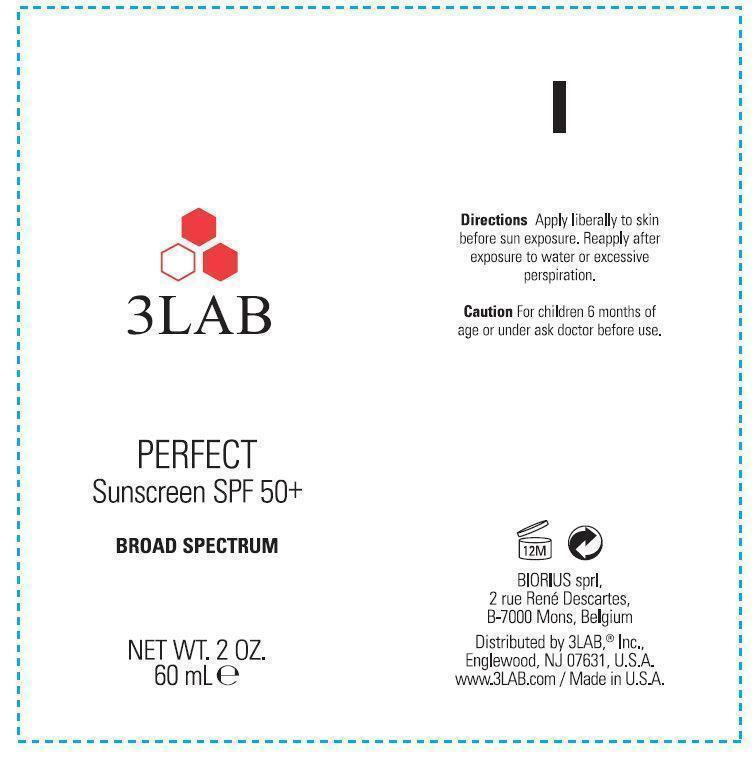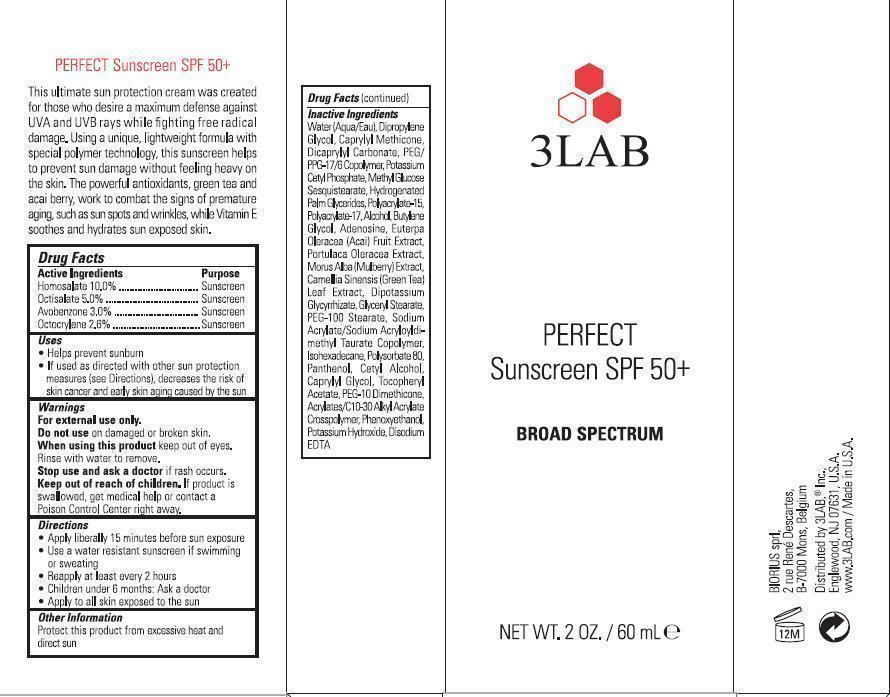 DRUG LABEL: 3LAB PERFECT Sunscreen SPF 50 Plus Broad Spectrum
NDC: 76159-345 | Form: CREAM
Manufacturer: 3LAB, Inc
Category: otc | Type: HUMAN OTC DRUG LABEL
Date: 20231212

ACTIVE INGREDIENTS: HOMOSALATE 100 mg/1 mL; OCTISALATE 50 mg/1 mL; AVOBENZONE 30 mg/1 mL; OCTOCRYLENE 26 mg/1 mL
INACTIVE INGREDIENTS: WATER; DIPROPYLENE GLYCOL; DICAPRYLYL CARBONATE; POTASSIUM CETYL PHOSPHATE; HYDROGENATED PALM GLYCERIDES; ALCOHOL; BUTYLENE GLYCOL; ADENOSINE; GREEN TEA LEAF; GLYCYRRHIZINATE DIPOTASSIUM; GLYCERYL MONOSTEARATE; PEG-100 STEARATE; ISOHEXADECANE; POLYSORBATE 80; PANTHENOL; CETYL ALCOHOL; CAPRYLYL GLYCOL; PHENOXYETHANOL; POTASSIUM HYDROXIDE; EDETATE DISODIUM

3LAB PERFECT Sunscreen SPF 50+ Broad Spectrum

Active Ingredients

Homosalate 10.0% Octisalate 5.0% Avobenzone 3.0% Octocrylene 2.6%

Purpose

Sunscreen

Uses

Helps prevent sunburn

If used ad directed with other sun protection measures (See Directions), decreases the risk of skin cancer and early skin aging caused by the sun

Warnings

For external use only

Do not use on damaged or broken skin.

When using this product keep out of eyes. Rinse with water to remove.

Stop use and ask a doctor if rash occurs.

Keep out of reach of children

If product is swallowed, get medical help or contact a Poison Control Center right away.

Directions

Apply liberally 15 minutes before sun exposure

Use a water resistant sunscreen if swimming or sweating

Reapply at least every 2 hours

Children under 6 months: Ask a doctor

Apply to all skin exposed to the sun

Other Information

Protect this product from excessive heat and direct sun

Inactive Ingredients

Water (Aqua/Eau), Dipropylene Glycol, Caprylyl Methicone, Dicaprylyl Carbonate, PEG/ PPG-17/6 Copolymer, Potassium Cetyl Phosphate, Methyl Glucose Sesquistearate, Hydrogenated Palm Glycerides, Polyacrylate-15, Polyacrylate-17, Alcohol, Butylene Glycol, Adenosine, Euterpa Oleracea (Acai) Fruit Extract, Portulaca Oleracea Extract, Morus Alba (Mulberry) Extract, Camellia Sinensis (Green Tea) Leaf Extract, Dipotassium Glycyrrhizate, Glyceryl Stearate, PEG-100 Stearate, Sodium Acrylate/Sodium Acryloyldimethyl Taurate Copolymer, Isohexadecane, Polysorbate 80, Panthenol, Cetyl Alcohol, Caprylyl Glycol, Tocopheryl Acetate, PEG-10 Dimethicone, Acrylates/C10-30 Alkyl Acrylate Crosspolymer, Phenoxyethanol, Potassium Hydroxide, Disodium EDTA

DESCRIPTION

This ultimate sun protection cream was created for those who desire a maximum defense against UVA and UVB rays while fighting free radical damage. Using a unique, lightweight formula with special polymer technology, this sunblock helps to prevent sun damage without feeling heavy on the skin. The powerful antioxidants, green tea and acai berry, work to combat the signs of premature aging, such as sun spots and wrinkles, while Vitamin E soothes and hydrates sun exposed skin.